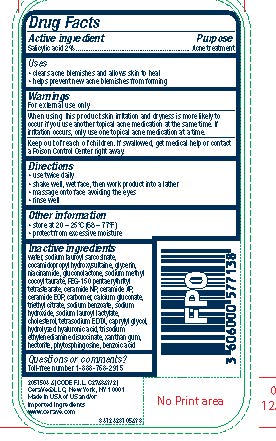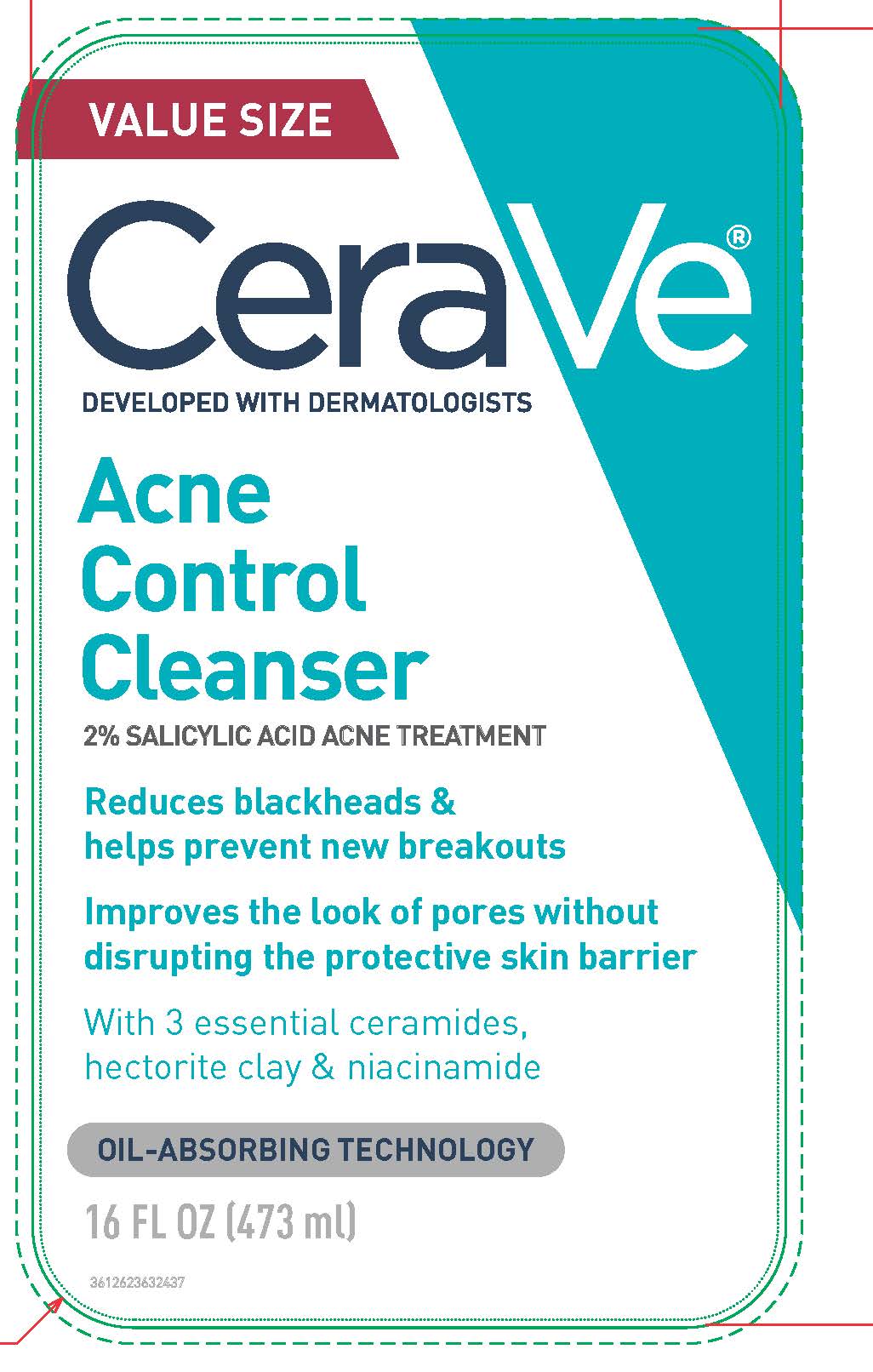 DRUG LABEL: CeraVe Developed with Dermatologists Acne Control Cleanser
NDC: 75897-112 | Form: GEL
Manufacturer: Unette Corporation
Category: otc | Type: HUMAN OTC DRUG LABEL
Date: 20240301

ACTIVE INGREDIENTS: SALICYLIC ACID 20 mg/1 mL
INACTIVE INGREDIENTS: WATER; SODIUM LAUROYL SARCOSINATE; COCAMIDOPROPYL HYDROXYSULTAINE; GLYCERIN; NIACINAMIDE; GLUCONOLACTONE; SODIUM METHYL COCOYL TAURATE; PEG-150 PENTAERYTHRITYL TETRASTEARATE; XANTHAN GUM; SODIUM BENZOATE; SODIUM HYDROXIDE; HECTORITE; TRISODIUM ETHYLENEDIAMINE DISUCCINATE; SODIUM LAUROYL LACTYLATE; EDETATE SODIUM; CALCIUM GLUCONATE; CERAMIDE NP; TRIETHYL CITRATE; CAPRYLYL GLYCOL; CERAMIDE AP; PHYTOSPHINGOSINE; CHOLESTEROL; HYALURONIC ACID; CARBOMER HOMOPOLYMER, UNSPECIFIED TYPE; BENZOIC ACID; CERAMIDE 1

CRV ACNE CONTROL CLEANSER 10ML SAMPLE

Active ingredient

Salicylic acid 2%

Purpose

Acne treatment

Uses

- clears acne blemishes and allows skin to heal
- helps prevent new acne blemishes from forming

Warnings

For external use only

When using this product

skin irritation and dryness is more likely to occur if you use another topical acne medication at the same time. if irritation occurs, only use one topical acne medication at a time.

Keep out of reach of children.

If swallowed, get medical help or contact a Poison Control Center right away.

Directions

- use twice daily
- shake well, wet face, then work product into a lather
- massage onto face avoiding the eyes
- rinse well

Inactive ingredients

water, sodium lauroyl sarcosinate, cocamidopropyl hydroxysultaine, glycerin, niacinamide, gluconolactone, sodium methyl cocoyl taurate, PEG-150 pentaerythrityl tetrastearate, xanthan gum, sodium benzoate, sodium hydroxide, hectorite, trisodium ethylenediamine disuccinate, sodium lauroyl lactylate, tetrasodium EDTA, calcium gluconate, ceramide NP, triethyl citrate, caprylyl glycol, ceramide AP, phytosphingosine, cholesterol, hydrolyzed hyaluronic acid, carbomer, benzoic acid, ceramide EOP